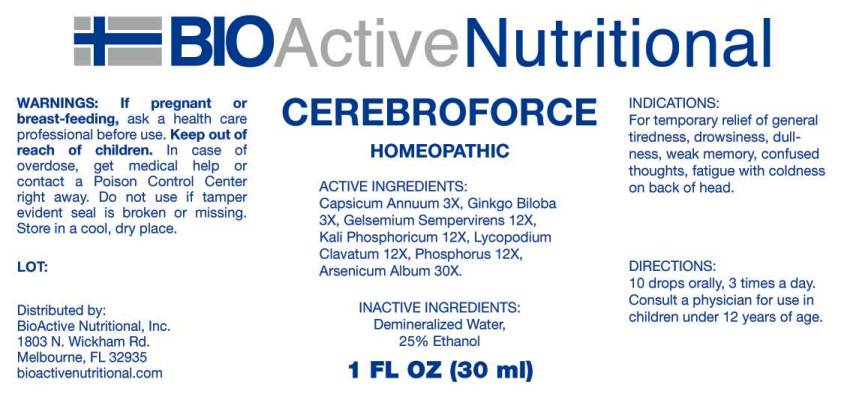 DRUG LABEL: Cerebroforce
NDC: 43857-0176 | Form: LIQUID
Manufacturer: BioActive Nutritional, Inc
Category: homeopathic | Type: HUMAN OTC DRUG LABEL
Date: 20160713

ACTIVE INGREDIENTS: CAPSICUM 3 [hp_X]/1 mL; GINKGO 3 [hp_X]/1 mL; GELSEMIUM SEMPERVIRENS ROOT 12 [hp_X]/1 mL; POTASSIUM PHOSPHATE, DIBASIC 12 [hp_X]/1 mL; LYCOPODIUM CLAVATUM SPORE 12 [hp_X]/1 mL; PHOSPHORUS 12 [hp_X]/1 mL; ARSENIC TRIOXIDE 30 [hp_X]/1 mL
INACTIVE INGREDIENTS: WATER; ALCOHOL

Drug Facts:

ACTIVE INGREDIENTS:

Capsicum Annuum 3X, Ginkgo Biloba 3X, Gelsemium Sempervirens 12X, Kali Phosphoricum 12X, Lycopodium Clavatum 12X, Phosphorus 12X, Arsenicum Album 30X.

INDICATIONS:

For temporary relief of general tiredness, drowsiness, dullness, weak memory, confused thoughts, fatigue with coldness on back of head.

WARNINGS:

If pregnant or breast-feeding, ask a health care professional before use.

Keep out of reach of children. In case of overdose, get medical help or contact a Poison Control Center right away.

Do not use if tamper evident seal is broken or missing.

Store in a cool, dry place.

Keep out of reach of children. In case of overdose, get medical help or contact a Poison Control Center right away.

DIRECTIONS:

10 drop orally, 3 times a day. Consult a physician for use in children under 12 years of age.

INDICATIONS:

For temporary relief of general tiredness, drowsiness, dullness, weak memory, confused thoughts, fatigue with coldness on back of head.

INACTIVE INGREDIENTS:

Demineralized Water, 25% Ethanol

QUESTIONS:

Distributed by:
BioActive Nutritional, Inc.
1803 N. Wickham Rd.
Melbourne, FL 32935
bioactivenutritional.com

PACKAGE LABEL DISPLAY:

BIOActive Nutritional

CEREBROFORCE

HOMEOPATHIC

1 FL OZ (30 ml)